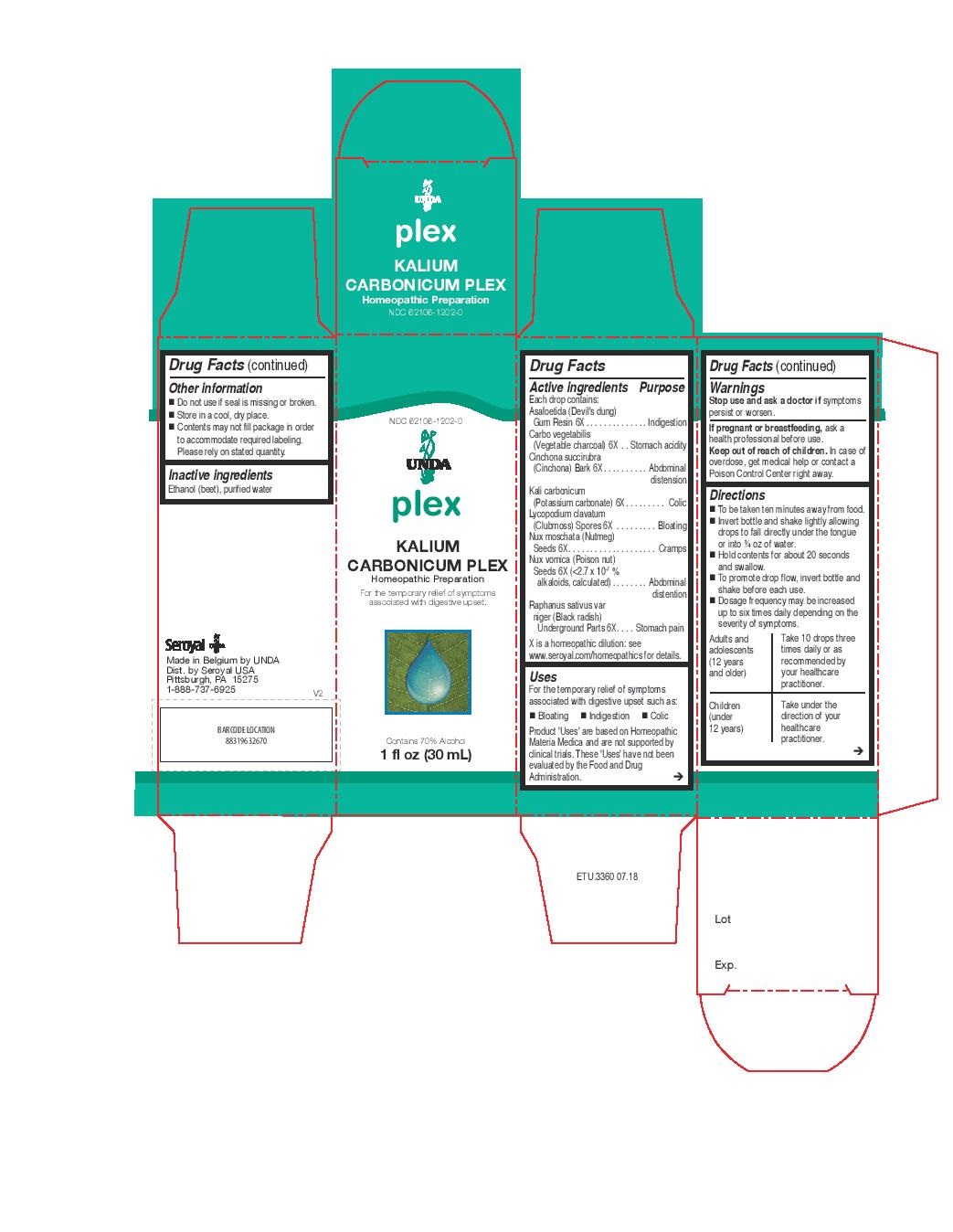 DRUG LABEL: KALIUM CARBONICUM PLEX
NDC: 62106-1202 | Form: LIQUID
Manufacturer: Seroyal USA
Category: homeopathic | Type: HUMAN OTC DRUG LABEL
Date: 20221109

ACTIVE INGREDIENTS: ASAFETIDA 6 [hp_X]/30 mL; ACTIVATED CHARCOAL 6 [hp_X]/30 mL; CINCHONA PUBESCENS BARK 6 [hp_X]/30 mL; NUTMEG 6 [hp_X]/30 mL; POTASSIUM CARBONATE 6 [hp_X]/30 mL; LYCOPODIUM CLAVATUM SPORE 6 [hp_X]/30 mL; STRYCHNOS NUX-VOMICA SEED 6 [hp_X]/30 mL; RAPHANUS SATIVUS 6 [hp_X]/30 mL
INACTIVE INGREDIENTS: ALCOHOL; WATER

KALIUM CARBONICUM PLEX

Active ingredients

Each drop contains:

Asafoetida (Devil's dung) Gum Resin 6X
Carbo vegetabilis (Vegetable charcoal) 6X
Cinchona succirubra (Cinchona) Bark 6X
Kali carbonicum (Potassium carbonate) 6X
Lycopodium clavatum (Clubmoss) Spores 6X
Nux moschata (Nutmeg) Seeds 6X
Nux vomica (Poison nut) Seeds 6X (<2.7 x 10-7 % alkaloids, calculated)
Raphanus sativus var niger (Black radish) Underground Parts 6X

Uses

For the temporary relief of symptoms associated with digestive upset such as:
Bloating

Indigestion

Colic

Warnings
Stop use and ask a doctor if symptoms persist or worsen.
If pregnant or breastfeeding, ask a health professional before use.
Keep out of reach of children.

In case of overdose, get medical help or contact a Poison Control Center right away.

Stop use and ask a doctor if symptoms persist or worsen.

PREGNANCY OR BREAST FEEDING

If pregnant or breastfeeding, ask a health professional before use.

Keep out of reach of children.

OVERDOSAGE

In case of overdose, get medical help or contact a Poison Control Center right away.

Inactive ingredients
Ethanol (beet), purified water

Other information
Do not use if seal is missing or broken.
Store in a cool, dry place.

Contents may not fill package in order to accommodate required labeling. Please rely on stated quantity

Directions
To be taken ten minutes away from food.
Invert bottle and shake lightly allowing drops to fall directly under the tongue or into ¼ oz of water.
Hold contents for about 20 seconds and swallow.
To promote drop flow, invert bottle and shake before each use.
Dosage frequency may be increased up to six times daily depending on the severity of symptoms.

Adults and adolescents (12 years and older)

Take 10 drops three times daily or as recommended by your healthcare practitioner.

Children (under 12 years)

Take under the direction of your healthcare practitioner.

Uses

For the temporary relief of symptoms associated with digestive upset such as:
Bloating

Indigestion

Colic

Directions
To be taken ten minutes away from food.
Invert bottle and shake lightly allowing drops to fall directly under the tongue or into ¼ oz of water.
Hold contents for about 20 seconds and swallow.
To promote drop flow, invert bottle and shake before each use.
Dosage frequency may be increased up to six times daily depending on the severity of symptoms.

Adults and adolescents (12 years and older)

Take 10 drops three times daily or as recommended by your healthcare practitioner.

Children (under 12 years)

Take under the direction of your healthcare practitioner.

PACKAGE LABEL

NDC 62106-1202-0

UNDA

plex

KALIUM CARBONICUM PLEX

Homeopathic Preparation

For the temporary relief of symptoms associated with digestive upset.

Contains 70% Alcohol
1 fl oz (30 mL)